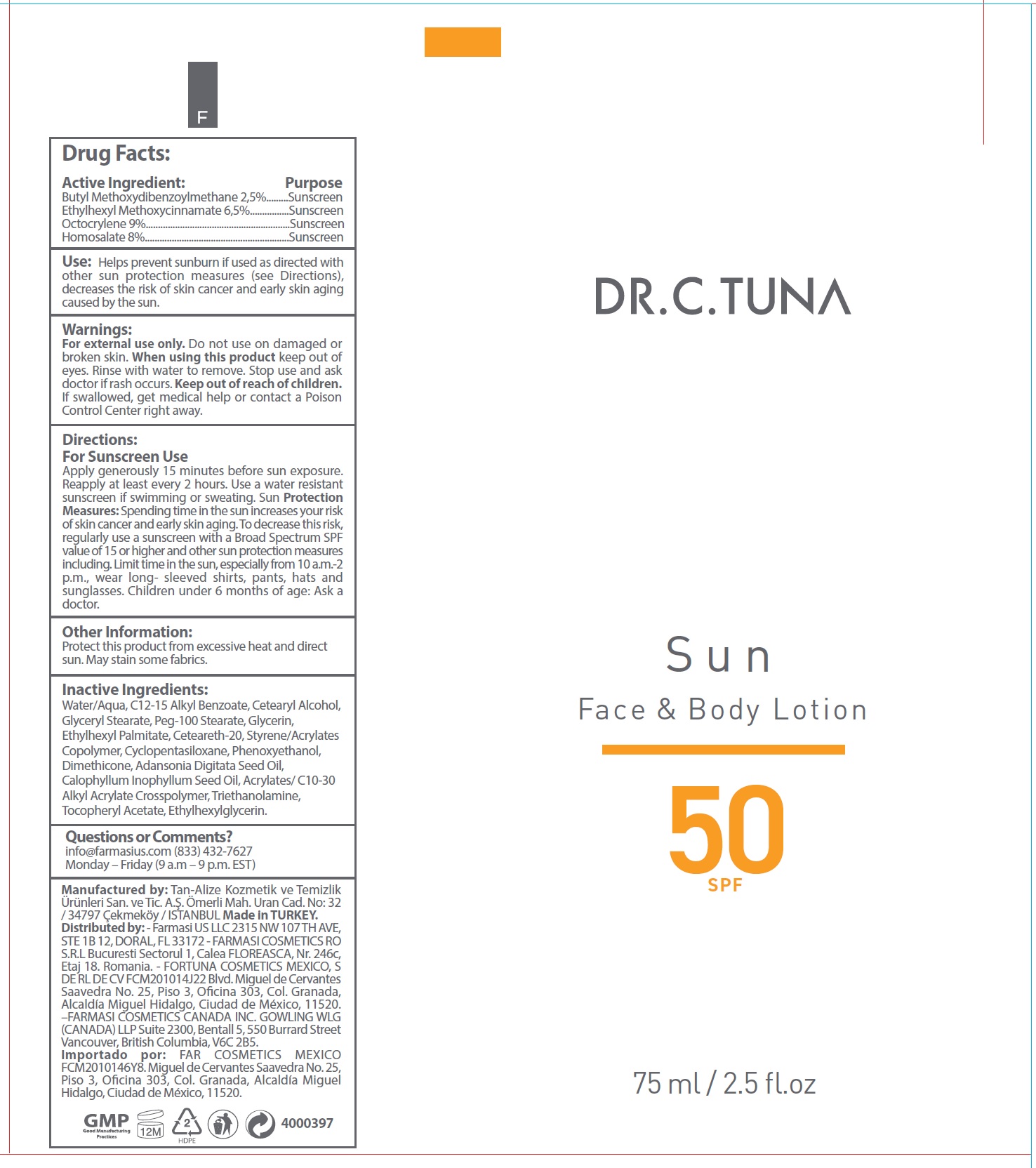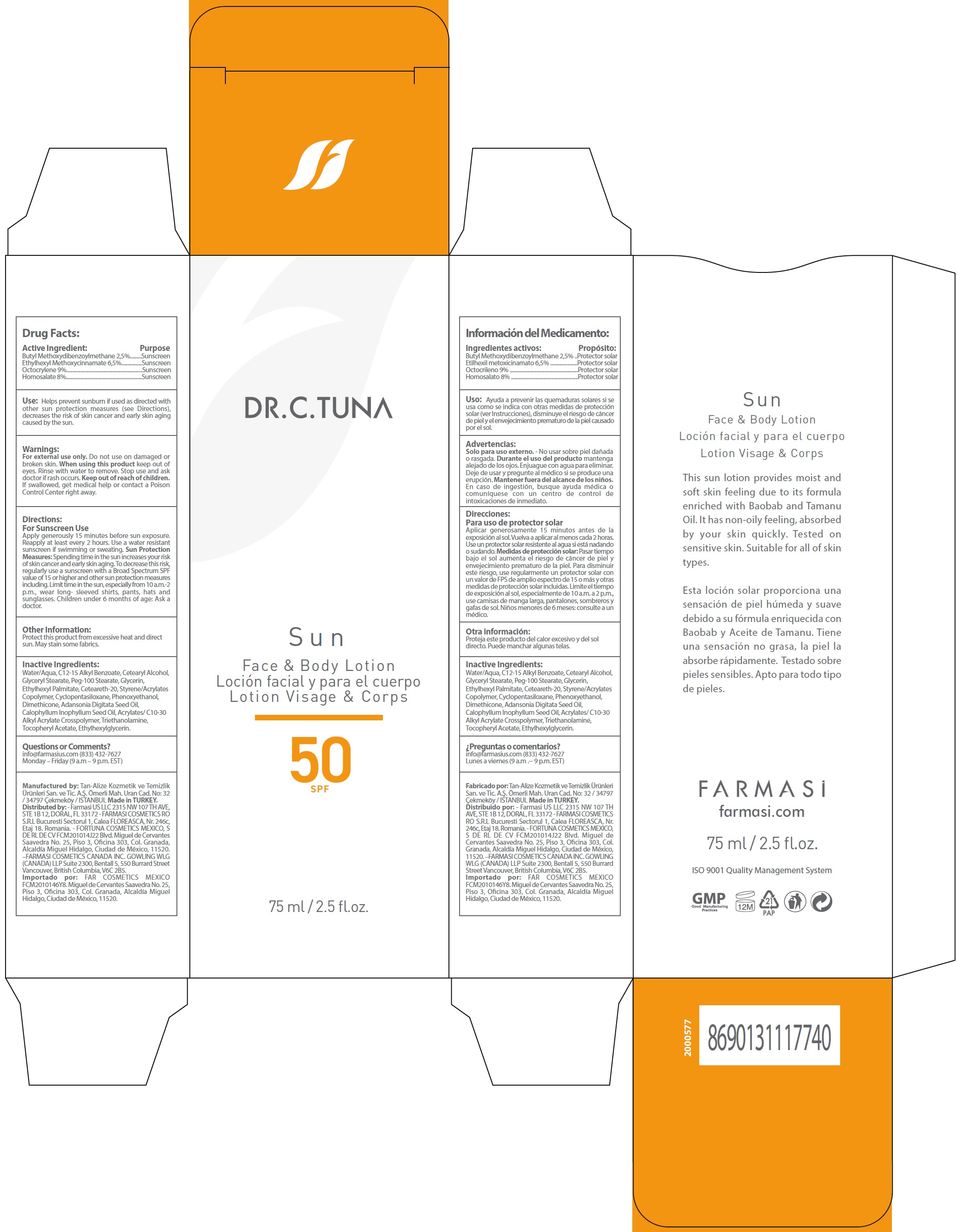 DRUG LABEL: Dr. C. Tuna Sun Face and Body SPF 50
NDC: 74690-015 | Form: LOTION
Manufacturer: Farmasi US LLC
Category: otc | Type: HUMAN OTC DRUG LABEL
Date: 20231105

ACTIVE INGREDIENTS: AVOBENZONE 25 mg/1 mL; OCTINOXATE 65 mg/1 mL; OCTOCRYLENE 90 mg/1 mL; HOMOSALATE 80 mg/1 mL
INACTIVE INGREDIENTS: WATER; ALKYL (C12-15) BENZOATE; CETOSTEARYL ALCOHOL; GLYCERYL MONOSTEARATE; PEG-100 STEARATE; GLYCERIN; ETHYLHEXYL PALMITATE; POLYOXYL 20 CETOSTEARYL ETHER; STYRENE; CYCLOMETHICONE 5; PHENOXYETHANOL; DIMETHICONE; ADANSONIA DIGITATA SEED OIL; TAMANU OIL; CARBOMER INTERPOLYMER TYPE A (ALLYL SUCROSE CROSSLINKED); TROLAMINE; .ALPHA.-TOCOPHEROL ACETATE; ETHYLHEXYLGLYCERIN

Dr. C. Tuna Sun Face & Body Lotion SPF 50

Active Ingredient:

Butyl Methoxydibenzoylmethane 2,5% Ethylhexyl Methoxycinnamate 6,5% Octocrylene 9% Homosalate 8%

Purpose

Sunscreen

Use:

Helps prevent sunburn if used as directed with other sun protection measures (see Directions), decreases the risk of skin cancer and early skin aging caused by the sun.

Warnings:

For external use only.

Do not use

on damaged or broken skin.

When using this product

keep out of eyes. Rinse with water to remove.

Stop use and ask doctor if

rash occurs.

Keep out of reach of children.

If swallowed, get medical help or contact a Poison Control Center right away.

Directions:

For Sunscreen Use

Apply generously 15 minutes before sun exposure. Reapply at least every 2 hours. Use a water resistant sunscreen if swimming or sweating. Spending time in the sun increases your risk of skin cancer and early skin aging. To decrease this risk, regularly use a sunscreen with a Broad Spectrum SPF value of 15 or higher and other sun protection measures including. Limit time in the sun, especially from 10 a.m.-2 p.m., wear long- sleeved shirts, pants, hats and sunglasses. Children under 6 months of age: Ask a doctor. Sun Protection Measures:

Other Information:

Protect this product from excessive heat and direct sun. May stain some fabrics.

Inactive Ingredients:

Water/Aqua, C12-15 Alkyl Benzoate, Cetearyl Alcohol, Glyceryl Stearate, Peg-100 Stearate, Glycerin, Ethylhexyl Palmitate, Ceteareth-20, Styrene/Acrylates Copolymer, Cyclopentasiloxane, Phenoxyethanol, Dimethicone, Adansonia Digitata Seed Oil, Calophyllum Inophyllum Seed Oil, Acrylates/ C10-30 Alkyl Acrylate Crosspolymer, Triethanolamine, Tocopheryl Acetate, Ethylhexylglycerin.

Questions or Comments?

info@farmasius.com (833) 432-7627

Monday – Friday (9 a.m – 9 p.m. EST)